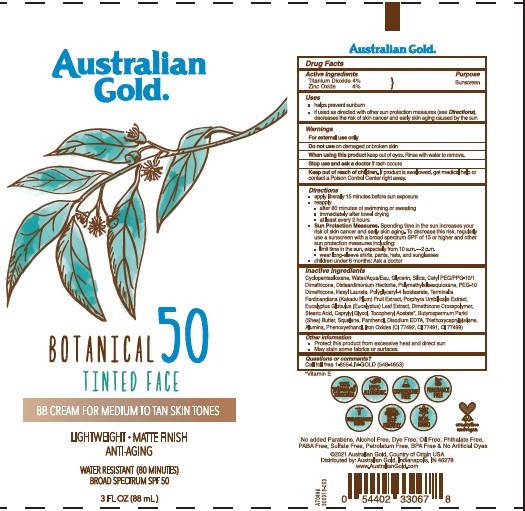 DRUG LABEL: Austalian Gold
NDC: 58443-0316 | Form: LOTION
Manufacturer: Prime Enterprises Inc.
Category: otc | Type: HUMAN OTC DRUG LABEL
Date: 20211028

ACTIVE INGREDIENTS: TITANIUM DIOXIDE 43.6 mg/1 mL; ZINC OXIDE 43.6 mg/1 mL
INACTIVE INGREDIENTS: TRIETHOXYCAPRYLYLSILANE; FERRIC OXIDE RED; PEG-10 DIMETHICONE (600 CST); CETYL PEG/PPG-10/1 DIMETHICONE (HLB 2); CYCLOMETHICONE 5; POLYGLYCERYL-4 ISOSTEARATE; DISTEARDIMONIUM HECTORITE; DIMETHICONE CROSSPOLYMER (450000 MPA.S AT 12% IN CYCLOPENTASILOXANE); PANTHENOL; ALUMINUM OXIDE; CAPRYLYL GLYCOL; STEARIC ACID; SQUALANE; SILICON DIOXIDE; POLYMETHYLSILSESQUIOXANE (4.5 MICRONS); PORPHYRA UMBILICALIS; GLYCERIN; KAKADU PLUM; PHENOXYETHANOL; ALPHA-TOCOPHEROL ACETATE; WATER; EUCALYPTUS GLOBULUS LEAF; SHEA BUTTER; EDETATE DISODIUM ANHYDROUS; HEXYL LAURATE

Australian Gold Botanical Sunscreen Tinted Face 50

Active Ingredients

Titanium Dioxide 4%

Zinc Oxide 4%

Purpose

Sunscreen

Uses

- helps prevent sunburn
  - if used as directed with other sun protection measures (see Directions) decreases the risk of skin cancer and early skin aging caused by the sun

Warnings

For external use only

Do not use on damaged or broken skin

When using this product keep out of eyes. Rinse with water to remove.

Stop use and ask a doctor if rash occurs

Keep out of reach of children. If product is swallowed, get medical help or contact a Poison Control Center right away.

Directions

- apply liberally 15 minutes before sun exposure
- reapply:
- after 80 minutes of swimming or sweating
- immediately after towel drying
- at least every 2 hours
- Sun Protection Measures Spending time ine the sun increases your risk of skin cancer and early skin aging. To decrease this risk, regularly use a sunscreen with a broad spectrum SPF valvue of 15 or higher and other sun protecion measures including:
- limit tim ein the sun, especially from 10am-2pm
- wear long sleeve shirts, pants, hats, and sunglasses
- children under 6 months: Ask a doctor

INACTIVE INGREDIENTS

Alumina, Butyrospermum Parkii (Shea) Butter, Caprylyl Glycol, Cetyl PEG/PPG-10/1 Dimethicone, Cyclopentasiloxane, Dimethicone Crosspolymer, Disodium EDTA, Disteardimonium Hectorite, Eucalyptus Globulus Leaf Extract, Glycerin, Hexyl Laurate, Iron Oxides, Panthenol, PEG-10 Dimethicone, Phenoxyethanol, Polyglyceryl-4 Isostearate, Polymethylsilsesquioxane, Porphyra Umbilicalis Extract, Silica, Squalane, Stearic Acid, Terminalia Ferdinandiana (Kakadu Plum) Fruit Extract, Tocopheryl Acetate, Triethoxycaprylylsilane, Water

Other Information

- Protect this product from excesive heat and direct sun
- May stain some frabics or surfaces

Questions or Comments?

Call toll free 1-855-LIV-GOLD (548-4653)